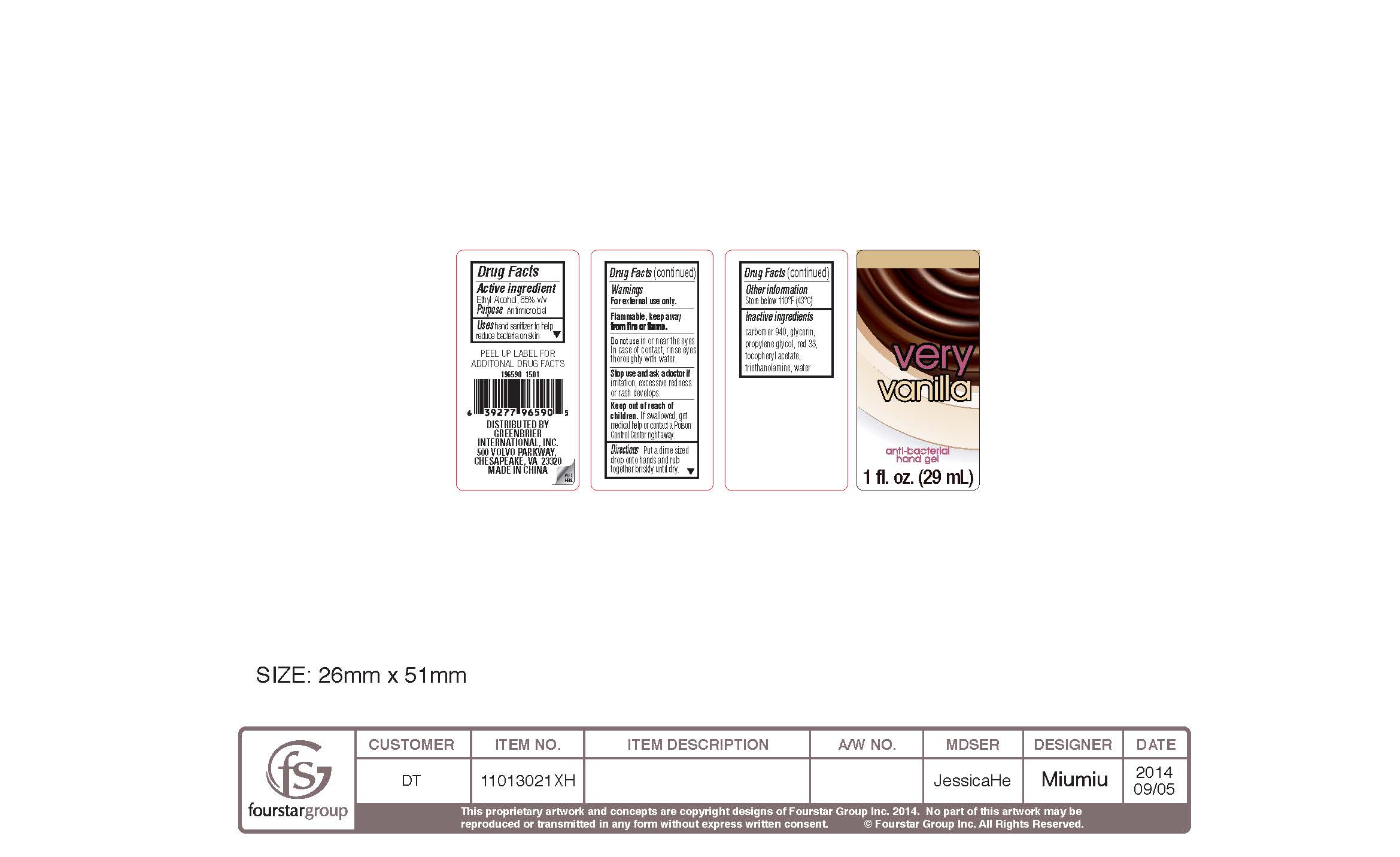 DRUG LABEL: ALCOHOL
                
NDC: 43473-805 | Form: GEL
Manufacturer: Nantong Health & Beyond Hygienic Products Inc.
Category: otc | Type: HUMAN OTC DRUG LABEL
Date: 20140901

ACTIVE INGREDIENTS: ALCOHOL 65 mL/100 mL
INACTIVE INGREDIENTS: CARBOMER HOMOPOLYMER TYPE C (ALLYL PENTAERYTHRITOL CROSSLINKED); GLYCERIN; PROPYLENE GLYCOL; D&C RED NO. 33; .ALPHA.-TOCOPHEROL ACETATE; TROLAMINE; WATER

Drug Facts

Inactive Ingredients

carbomer 940, glycerin,

propylene glycol, red 33,

tocopheryl acetate,

triethonamoline, water

Active Ingredient

Ethyl Alcohol, 65 % v/v

Purpose Antimicrobial

Warnings

For external use only

Keep out of reach of children. If swallowed,

get medical help or contact a Poison

Control Center right away.

DOSAGE AND ADMINISTRATION

Directions. Put a dime sized

drop onto hands and rub

briskly until dry.

INDICATIONS AND USAGE

Uses. hand sanitizer to help

reduce bacteria on skin

Do not use in or near the eyes.

In case of contact, rinse eyes

thoroughly with water.

OTHER SAFETY INFORMATION

Flammable. Keep away from

fire or flame

Stop use and ask a doctor

if irritation, excessive redness

or rash develops

Other information

Store below 110 F (43 C)